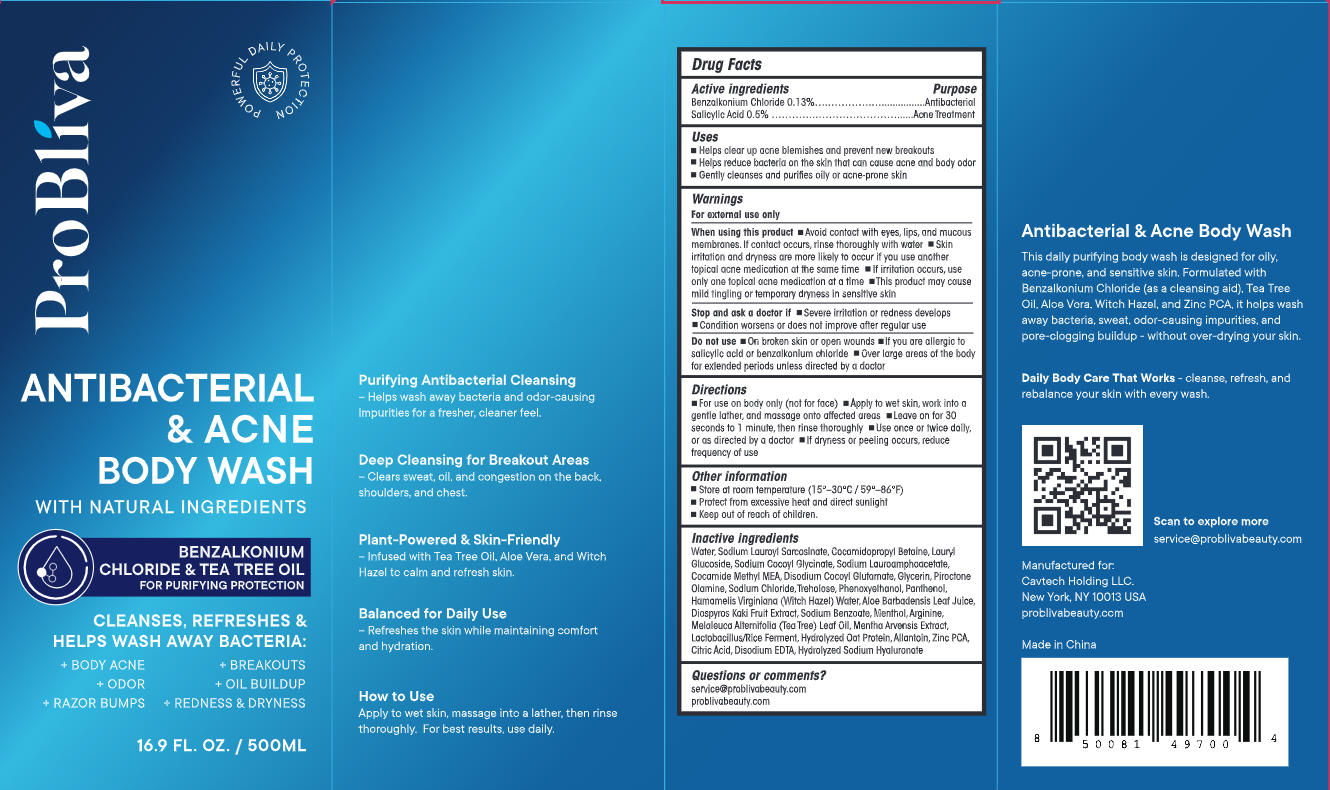 DRUG LABEL: ProBliva Antibacterial and Acne Body Wash
NDC: 85464-004 | Form: SHAMPOO
Manufacturer: CAVTECH HOLDING LLC
Category: otc | Type: HUMAN OTC DRUG LABEL
Date: 20260128

ACTIVE INGREDIENTS: BENZALKONIUM CHLORIDE 0.65 g/500 g; SALICYLIC ACID 2.5 g/500 g
INACTIVE INGREDIENTS: SODIUM CHLORIDE; ALOE BARBADENSIS LEAF JUICE; ZINC PCA; MENTHA ARVENSIS LEAF OIL; SODIUM LAUROYL SARCOSINATE; MENTHOL; ALLANTOIN; WATER; LAURYL GLUCOSIDE; DISODIUM COCOYL GLUTAMATE; HUMAN GHRELIN O-ACYLTRANSFERASE; DIOSPYROS KAKI FRUIT; ARGININE; GLYCERIN; PHENOXYETHANOL; COCAMIDE METHYL MEA; SODIUM BENZOATE; TREHALOSE; COCAMIDOPROPYL BETAINE; LACTOBACILLUS; HAMAMELIS VIRGINIANA ROOT BARK/STEM BARK; CITRIC ACID; SODIUM COCOYL GLYCINATE; MAGNESIUM DISODIUM EDTA; SODIUM LAUROAMPHOACETATE; PIROCTONE OLAMINE; HYDROLYZED SODIUM HYALURONATE 10; MELALEUCA ALTERNIFOLIA (TEA TREE) LEAF OIL

ProBliva Antibacterial & Acne Body Wash-85464-004-01

ACTIVE INGREDIENT

Benzalkonium Chloride 0.13%

Salicylic Acid 0.5%

PURPOSE

Antibacterial

Acne Treatment

DOSAGE AND ADMINISTRATION

- Helps clear up acne blemishes and prevent new breakouts
- Helps reduce bacteria on the skin that can cause acne and body odor
- Gently cleanses and purifies oily or acne-prone skin

WARNINGS

Fore external use only

WHEN USING

- Avoid contact with eyes, lips, and mucous membranes. If contact occurs, rinse thoroughly with water
- Skin irritation and dryness are more likely to occur If you use another topical acne medication at the same time
- If irritation occurs, useonly one fopical acne medication at a time
- This product may causemild tingling or temporary dryness in sensitive skin

ASK DOCTOR

- Stop and ask a doctor if -Severe irrifation or redness develops
- Condition worsens or does not improve after regular use

DO NOT USE

- On broken skin or open wounds
- lf you are allergic tosalicylic acid or benzalkonium chloride
- Over large areas of the bodyfor extended periods unless directed by a doctor

INDICATIONS AND USAGE

- For use on body only (not for face)
- Apply to wet skin, work into agentle lather, and massage onto affected areas
- Leave on for 30seconds to 1 minute, then rinse thoroughly
- Use once or twice daily,or as directed by a doctor
- If dryness or peeling occurs, reduce frequency of use

OTHER SAFETY INFORMATION

- Store at room temperature (15°-30°C/59°-86°F)
- Protect from excessive heat and direct sunlight
- Keep out of reach of children.

INACTIVE INGREDIENT

Water, Sodium Lauroyl Sarcosinate, Cocamidopropyl Betaine, Lauryl Glucoside, Sodium Cocoyl Glycinate, Sodium Lauroamphoacetate,Cocamide Methyl MEA, Disodium Cocoyl Glutamate, Glycerin, Piroctone Olamine, Sodiumn Chloride, Trehalose, Phenoxyethanol, Panthenol,Hamamells Virginiana (Witch Hazel) Water, Aloe Barbadensis Leaf Julce,Diospyros Kaki Fruit Extract, Sodium Benzoate, Menthol, Arginine,Melaleuca Alternifolia (Tea Tree) Leaf Oil, Mentha Arvensis Extract,Lactobacillus/Rice Ferment, Hydrolyzed Oat Protein, Allantoin, Zinc PCA,Citric Acid, Disodium EDTA, Hydrolyzed Sodium Hyaluronate

QUESTIONS

service@problivabeauty.com

problivabeauty.com

Keep out of reach of children section.